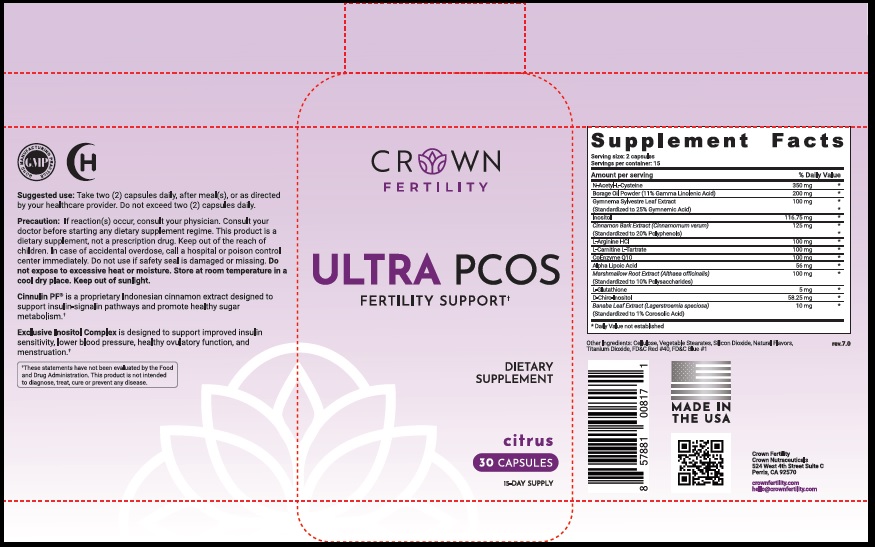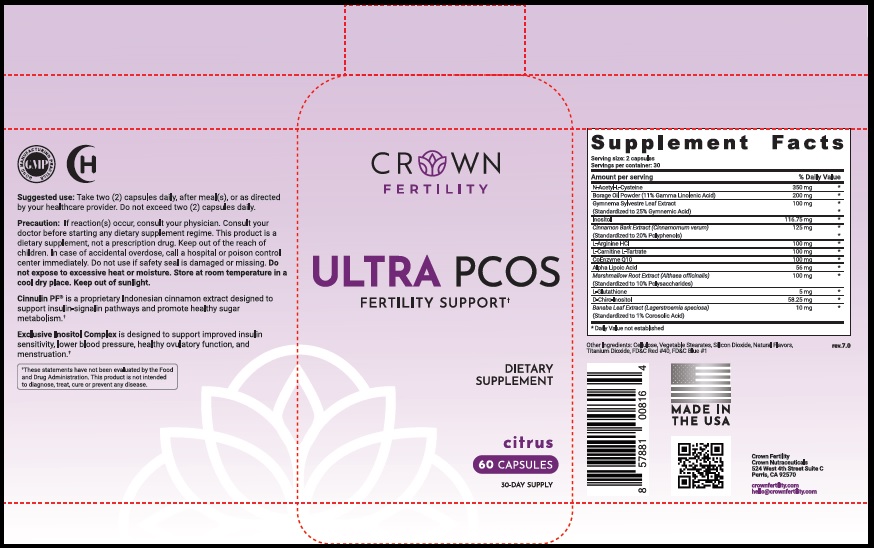 DRUG LABEL: ULTRA PCOS CITRUS
NDC: 73489-006 | Form: CAPSULE
Manufacturer: CROWN GENERAL AGENCY INC
Category: other | Type: Dietary Supplement
Date: 20211022

ACTIVE INGREDIENTS: ACETYLCYSTEINE 350 mg/1 1; GAMOLENIC ACID 200 mg/1 1; GYMNEMA SYLVESTRE LEAF 100 mg/1 1; INOSITOL 116.75 mg/1 1; CHINESE CINNAMON 125 mg/1 1; ARGININE HYDROCHLORIDE 100 mg/1 1; LEVOCARNITINE TARTRATE 100 mg/1 1; UBIDECARENONE 100 mg/1 1; THIOCTIC ACID 56 mg/1 1; ALTHAEA OFFICINALIS ROOT 100 mg/1 1; GLUTATHIONE 5 mg/1 1; CHIRO-INOSITOL, (+)- 58.25 mg/1 1; LAGERSTROEMIA SPECIOSA WHOLE 10 mg/1 1
INACTIVE INGREDIENTS: POWDERED CELLULOSE; MAGNESIUM STEARATE; SILICON DIOXIDE; TITANIUM DIOXIDE; FD&C RED NO. 40; FD&C BLUE NO. 1

STATEMENT OF IDENTITY

Dietary Supplement

Suggested Use

Take two (2) capsules daily, after meal(s), or as directed by your healthcare provider. Do not exceed two (2) capsules daily.

Precaution

If reaction(s) occur, consult your physician. Consult your doctor before starting any dietary supplement regime. This product is a dietary supplement, not a prescription drug. Keep out of the reach of children. In case of accidental overdose, call a hospital or poison control center immediately. Do not use if safety seal is damaged or missing. Do not expose to excessive heat or moisture. Store at room temperature in a cool dry place. Keep out of sunlight.